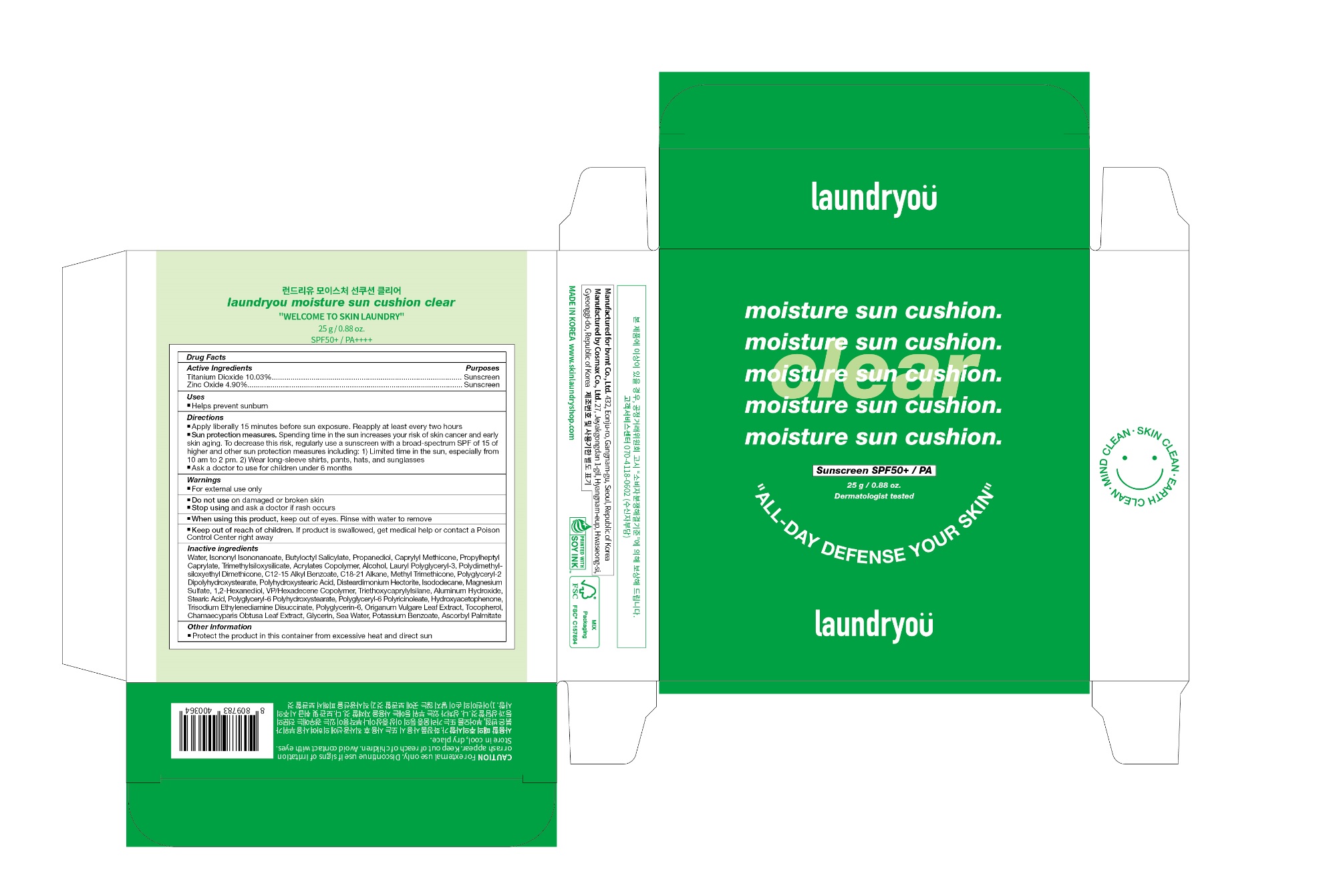 DRUG LABEL: LAUNDRYOU MOISTURE SUN CUSHION CLEAR
NDC: 83024-001 | Form: CREAM
Manufacturer: bvmt Co.,Ltd.
Category: otc | Type: HUMAN OTC DRUG LABEL
Date: 20221005

ACTIVE INGREDIENTS: TITANIUM DIOXIDE 10.03 g/100 g; ZINC OXIDE 4.9 g/100 g
INACTIVE INGREDIENTS: WATER; ISONONYL ISONONANOATE; BUTYLOCTYL SALICYLATE; PROPANEDIOL; CAPRYLYL TRISILOXANE; PROPYLHEPTYL CAPRYLATE; TRIMETHYLSILOXYSILICATE (M/Q 0.6-0.8); BUTYL ACRYLATE/METHYL METHACRYLATE/METHACRYLIC ACID COPOLYMER (18000 MW); ALCOHOL; ALKYL (C12-15) BENZOATE; C18-C21 ALKANE; METHYL TRIMETHICONE; POLYGLYCERYL-2 DIPOLYHYDROXYSTEARATE; POLYHYDROXYSTEARIC ACID (2300 MW); DISTEARDIMONIUM HECTORITE; ISODODECANE; MAGNESIUM SULFATE, UNSPECIFIED FORM; 1,2-HEXANEDIOL; VINYLPYRROLIDONE/HEXADECENE COPOLYMER; TRIETHOXYCAPRYLYLSILANE; ALUMINUM HYDROXIDE; STEARIC ACID; POLYGLYCERYL-6 POLYRICINOLEATE; HYDROXYACETOPHENONE; TRISODIUM ETHYLENEDIAMINE DISUCCINATE; POLYGLYCERIN-6; OREGANO; TOCOPHEROL; CHAMAECYPARIS OBTUSA LEAF; GLYCERIN; SODIUM CHLORIDE; POTASSIUM BENZOATE; ASCORBYL PALMITATE

83024-001_LAUNDRYOU MOISTURE SUN CUSHION CLEAR

ACTIVE INGREDIENT

Titanium Dioxide 10.03%

Zinc Oxide 4.90%

PURPOSE

Sunscreen

INDICATIONS AND USAGE

Helps prevent sunburn

DOSAGE AND ADMINISTRATION

Apply liberally 15 minutes before sun exposure. Reapply at least every two hours

Sun protection measures. Spending time in the sun increases your risk of skin cancer and early skin aging. To decrease this risk, regularly use a sunscreen with a broad spectrum SPF of 15 of higher and other sun protection measures including: 1) Limited time in the sun, especially from 10 am to 2 pm. 2) Wear long-sleeve shirts, pants, hats, and sunglasses

Ask a doctor to use for children under 6 months

WARNINGS

For external use only

Do not use on damaged or broken skin

Stop using and ask a doctor if rash occurs

When using this product, keep out of eyes. Rinse with water to remove

Keep out of reach of children. If product is swallowed, get medical help or contact a Poison Control Center right away

INACTIVE INGREDIENT

Water, Isononyl Isononanoate, Butyloctyl Salicylate, Propanediol, Caprylyl Methicone, Propylheptyl Caprylate, Trimethylsiloxysilicate, Acrylates Copolymer, Alcohol, Lauryl Polyglyceryl-3, Polydimethylsiloxyethyl Dimethicone, C12-15 Alkyl Benzoate, C18-21 Alkane, Methyl Trimethicone, Polyglyceryl-2 Dipolyhydroxystearate, Polyhydroxystearic Acid, Disteardimonium Hectorite, Isododecane, Magnesium Sulfate, 1,2-Hexanediol, VP/Hexadecene Copolymer, Triethoxycaprylylsilane, Aluminum Hydroxide, Stearic Acid, Polyglyceryl-6 Polyhydroxystearate, Polyglyceryl-6 Polyricinoleate, Hydroxyacetophenone, Trisodium Ethylenediamine Disuccinate, Polyglycerin-6, Origanum Vulgare Leaf Extract, Tocopherol, Chamaecyparis Obtusa Leaf Extract, Glycerin, Sea Water, Potassium Benzoate, Ascorbyl Palmitate